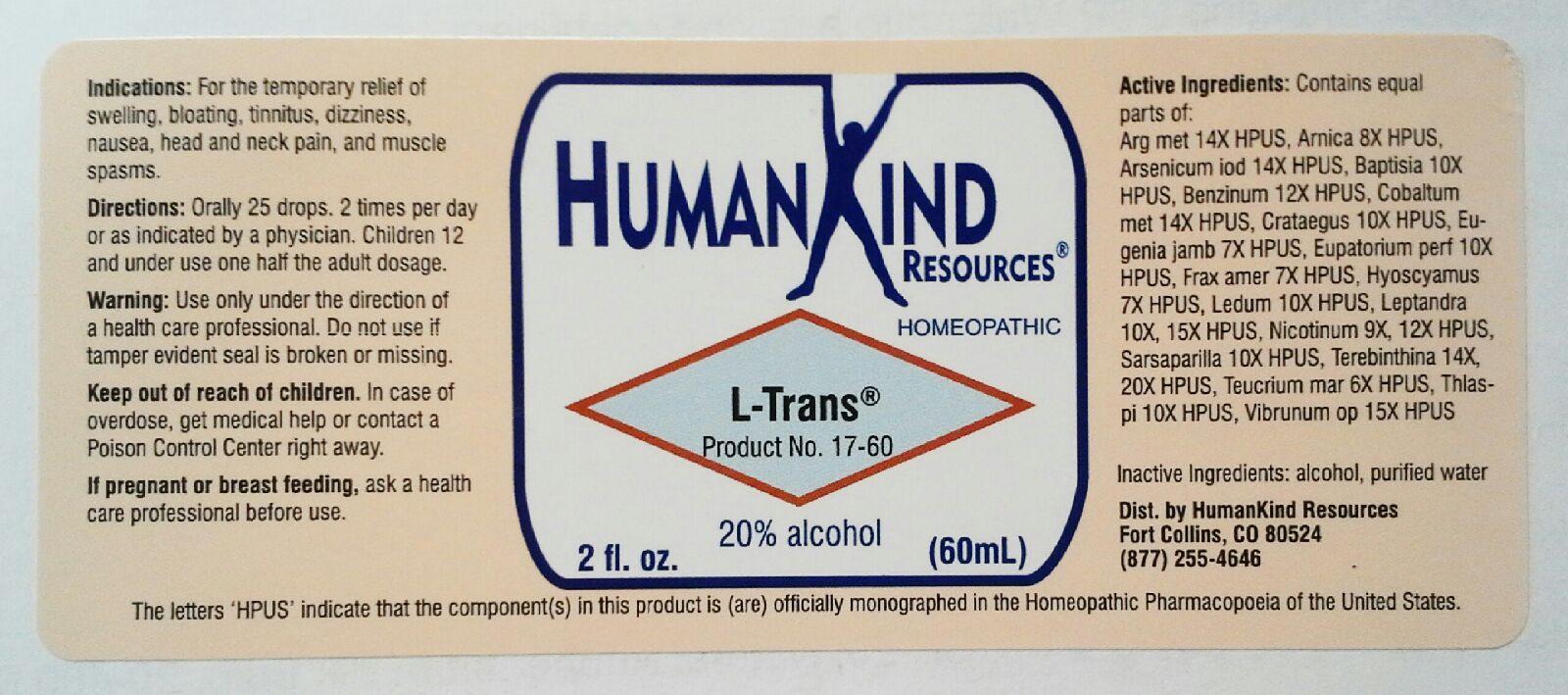 DRUG LABEL: L-Trans
NDC: 64616-095 | Form: LIQUID
Manufacturer: Vitality Works, Inc.
Category: homeopathic | Type: HUMAN OTC DRUG LABEL
Date: 20251217

ACTIVE INGREDIENTS: EUPATORIUM PERFOLIATUM FLOWERING TOP 10 [hp_X]/1 mL; FRAXINUS AMERICANA BARK 7 [hp_X]/1 mL; HYOSCYAMUS NIGER 7 [hp_X]/1 mL; LEDUM PALUSTRE TWIG 10 [hp_X]/1 mL; VERONICASTRUM VIRGINICUM ROOT 15 [hp_X]/1 mL; NICOTINE 12 [hp_X]/1 mL; SARSAPARILLA 10 [hp_X]/1 mL; TURPENTINE OIL 20 [hp_X]/1 mL; TEUCRIUM MARUM 6 [hp_X]/1 mL; CAPSELLA BURSA-PASTORIS 10 [hp_X]/1 mL; VIBURNUM OPULUS BARK 15 [hp_X]/1 mL; SILVER 14 [hp_X]/1 mL; ARNICA MONTANA 8 [hp_X]/1 mL; ARSENIC TRIIODIDE 14 [hp_X]/1 mL; BAPTISIA TINCTORIA 10 [hp_X]/1 mL; BENZENE 12 [hp_X]/1 mL; COBALT 14 [hp_X]/1 mL; CRATAEGUS FRUIT 10 [hp_X]/1 mL; SYZYGIUM JAMBOS SEED 7 [hp_X]/1 mL
INACTIVE INGREDIENTS: ALCOHOL; WATER

L-Trans

L-Trans

Argentum Metallicum 14X Eugenia Jambosa 7X Sarsparilla 10X

Arnica Montana Radix 8X Eupatorium Perfoliatum 10X Terebinthina 14X, 20X

Arsenicum Iodatum 14X Faxinus Americana 7X Teucrium Marum 6X

Baptisia Tinc 10X Hyoscyamus Nig Tinc 7X Thlaspi Bursa Pastorius 10X

Benzinum 12X Ledum Palustre 10X Vibrunum Opulus 15X

Cobaltum Metallicum 14X Leptandra Virginica 10X, 15X

Crataegus Oxyacantha 10X Nicotinum 9X, 12X

L-Trans

Alcohol, Purified Water

L-Trans

Use only under the direction of a health care professional. Do not use if tamper evident seal is broken or missing.

L-Trans

Keep out of reach of children. In case of overdose, get medical help or contact a Poison Control Center right away.

L-Trans

For the temporary relief of swelling, bloating, tinnitus, dizziness, nausea, head and neck pain, and muscle spasms.

L-Trans

Orally 25 drops, 2 times per day or as indicated by a physician. Children 12 and under use one half the adult dosage.

L-Trans

Aids movement and vitality within the lymphatic system.